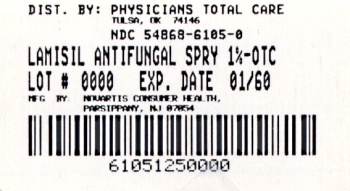 DRUG LABEL: Lamisil
NDC: 54868-6105 | Form: SPRAY
Manufacturer: Physicians Total Care, Inc.
Category: otc | Type: HUMAN OTC DRUG LABEL
Date: 20100101

ACTIVE INGREDIENTS: TERBINAFINE HYDROCHLORIDE 1.25 mL/125 mL
INACTIVE INGREDIENTS: ALCOHOL; POLYOXYL 20 CETOSTEARYL ETHER; PROPYLENE GLYCOL; WATER

Drug Facts

Active ingredient

Terbinafine hydrochloride

Purpose

Antifungal

Uses

- cures most jock itch (tinea cruris)
- relieves itching, burning, cracking, and scaling which accompany this condition

Warnings

For external use only

Do Not Use

- on nails or scalp
- in or near the mouth or the eyes
- for vaginal yeast infections

When using this product

do not get into eyes. If contact occurs, rinse eyes thoroughly with water.

Stop use and ask a doctor

if too much irritation occurs or gets worse.

Keep Out of Reach of Children

If swallowed, get medical help or contact a Poison Control

Center right away.

Directions

- adults and children 12 years and over
  - wash the affected area with soap and water and dry completely before applying
  - to open remove clear cap.
  - hold can 4" to 6" from skin. Press and hold to spray a thin layer over affected area
  - spray affected area once a day (morning or night) for 1 week or as directed by a doctor
  - release to stop spray
  - wipe excess from spray opening after each use
  - return cap to can
  - wash hands after each use
- children under 12 years: ask a doctor

Other information

store at 8° - 25° C (46° - 77° F)

Additional Information

Full Prescription Strength

Continuous Spray Action

Cures Most Jock Itch

For Effective Relief of Itching & Burning

Distr. By:

Novartis Consumer Health, Inc.
Parsippany, NJ 07054-0622 ©2009

Inactive ingredients

Ethanol, polyoxyl 20 cetostearyl ether, propylene glycol, purified water

Questions

call 1-800-452-0051 or visit us at www.lamisilat.com

Principal Display

Relabeling of "Additional Barcode" by:
Physicians Total Care, Inc.
Tulsa, OK 74146

NDC 54868-6105-0